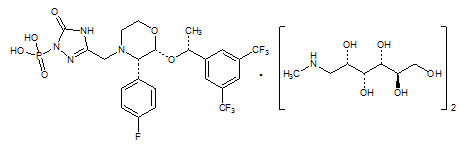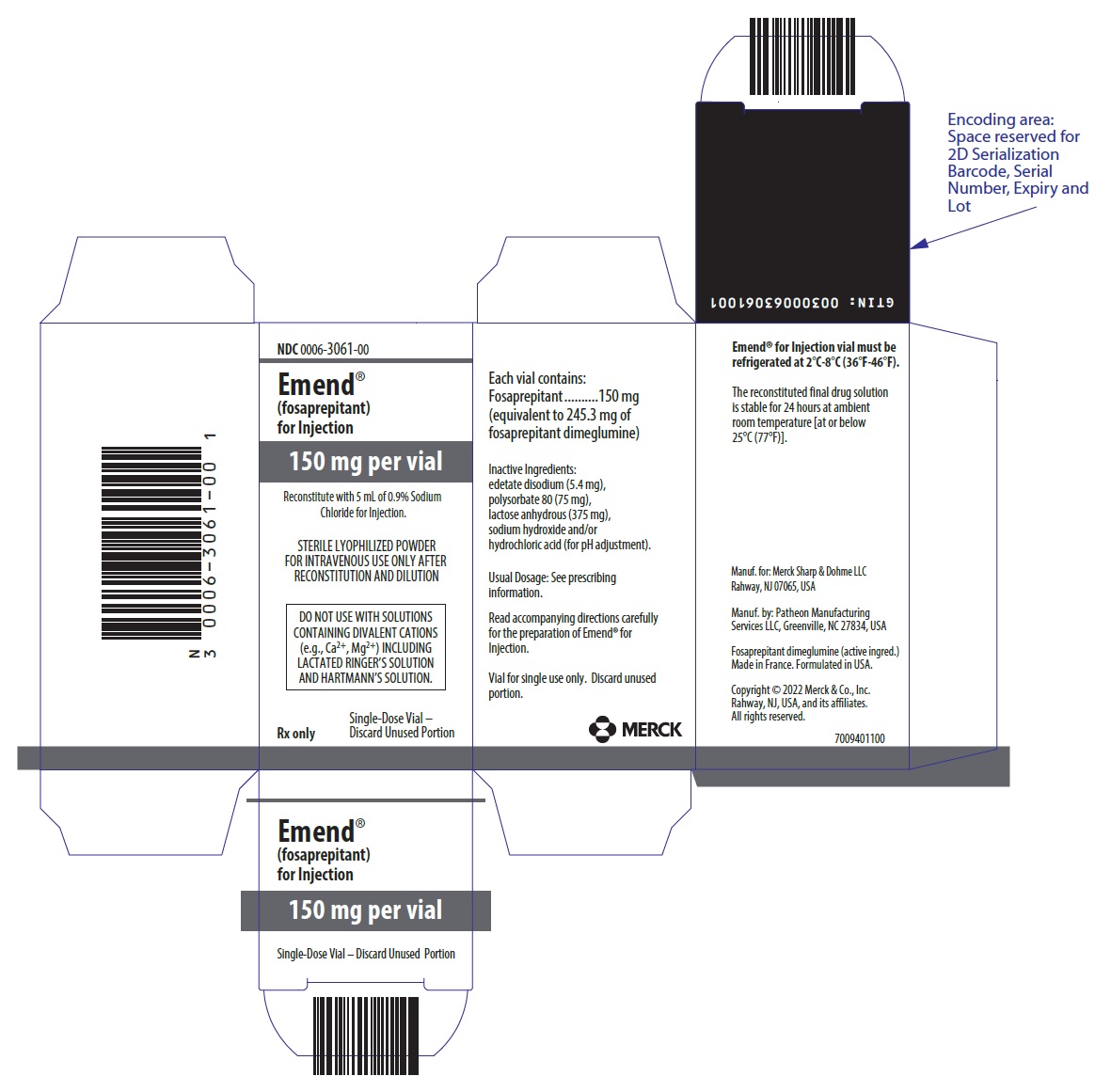 DRUG LABEL: EMEND
NDC: 0006-3061 | Form: INJECTION, POWDER, LYOPHILIZED, FOR SOLUTION
Manufacturer: Merck Sharp & Dohme LLC
Category: prescription | Type: HUMAN PRESCRIPTION DRUG LABEL
Date: 20220502

ACTIVE INGREDIENTS: FOSAPREPITANT DIMEGLUMINE 150 mg/5 mL
INACTIVE INGREDIENTS: EDETATE DISODIUM 5.4 mg/5 mL; HYDROCHLORIC ACID; ANHYDROUS LACTOSE 375 mg/5 mL; POLYSORBATE 80 75 mg/5 mL; SODIUM HYDROXIDE

HIGHLIGHTS OF PRESCRIBING INFORMATION

These highlights do not include all the information needed to use EMEND FOR INJECTION safely and effectively. See full prescribing information for EMEND FOR INJECTION.
EMEND (fosaprepitant) for injection, for intravenous use
Initial U.S. Approval: 2008

RECENT MAJOR CHANGES

Dosage and Administration (2.2) | 5/2022

1 INDICATIONS AND USAGE

EMEND® for injection is a substance P/neurokinin-1 (NK1) receptor antagonist, indicated in adults and pediatric patients 6 months of age and older, in combination with other antiemetic agents, for the prevention of (1):

- acute and delayed nausea and vomiting associated with initial and repeat courses of highly emetogenic cancer chemotherapy (HEC) including high-dose cisplatin.
- delayed nausea and vomiting associated with initial and repeat courses of moderately emetogenic cancer chemotherapy (MEC).

Limitations of Use (1)

- EMEND has not been studied for treatment of established nausea and vomiting.

2 DOSAGE AND ADMINISTRATION

Recommended Adult Dosage (2.1)

- EMEND for injection 150 mg on Day 1 as an intravenous infusion over 20 to 30 minutes. (2.1)
- Complete the infusion approximately 30 minutes prior to chemotherapy.

Recommended Dosage for Pediatric Patients (6 months to 17 years) Weighing at Least 6 kg (2.2)

- See Full Prescribing Information for pediatric dosage regimens by age.
- For single dose chemotherapy regimens: single dose of EMEND for injection on Day 1.
- For single- or multi-day chemotherapy regimens: 3-day EMEND regimen of EMEND for injection on Days 1, 2, and 3. EMEND capsules or EMEND for oral suspension may be used as an alternative on Days 2 and 3.
- Administer EMEND for injection through a central venous catheter as an intravenous infusion over 30 minutes (12 years to 17 years) or 60 minutes (6 months to less than 12 years).
- Complete the infusion approximately 30 minutes prior to chemotherapy.

Concomitant Antiemetics

- See Full Prescribing Information for additional information. (2.1, 2.2)

3 DOSAGE FORMS AND STRENGTHS

EMEND for injection: 150 mg fosaprepitant, lyophilized powder in single-dose vial for reconstitution. (3)

4 CONTRAINDICATIONS

- Known hypersensitivity to any component of this drug. (4, 5.2)
- Concurrent use with pimozide. (4)

5 WARNINGS AND PRECAUTIONS

- CYP3A4 Interactions: Fosaprepitant is a weak inhibitor of CYP3A4, and aprepitant, the active moiety, is a substrate, inhibitor, and inducer of CYP3A4; see Full Prescribing Information for recommendations regarding contraindications, risk of adverse reactions, and dosage adjustment of EMEND and concomitant drugs. (4, 5.1, 7.1, 7.2)
- Hypersensitivity Reactions (including anaphylaxis and anaphylactic shock): May occur during or soon after infusion. If symptoms occur, discontinue the drug. Do not reinitiate EMEND if symptoms occur with previous use. (4, 5.2)
- Infusion Site Reactions (including thrombophlebitis, necrosis, and vasculitis): Majority of reactions reported in patients receiving vesicant chemotherapy. Avoid infusion into small veins. Discontinue infusion and administer treatment if a severe reaction develops. (5.3)
- Warfarin (a CYP2C9 substrate): Risk of decreased INR of prothrombin time; monitor INR in 2–week period, particularly at 7 to 10 days, following initiation of EMEND. (5.4, 7.1)
- Hormonal Contraceptives: Efficacy of contraceptives may be reduced during and for 28 days following administration of EMEND. Use effective alternative or back-up methods of contraception. (5.5, 7.1, 8.3)

6 ADVERSE REACTIONS

- Most common adverse reactions in adults (≥2%) are: fatigue, diarrhea, neutropenia, asthenia, anemia, peripheral neuropathy, leukopenia, dyspepsia, urinary tract infection, pain in extremity. (6.1)
- Adverse reactions in pediatrics are similar to adults.

To report SUSPECTED ADVERSE REACTIONS, contact Merck Sharp & Dohme LLC at 1-877-888-4231 or FDA at 1-800-FDA-1088 or www.fda.gov/medwatch .

7 DRUG INTERACTIONS

See Full Prescribing Information for a list of clinically significant drug interactions. (4, 5.1, 5.4, 5.5, 7.1, 7.2)

FULL PRESCRIBING INFORMATION

1 INDICATIONS AND USAGE

EMEND® for injection, in combination with other antiemetic agents, is indicated in adults and pediatric patients 6 months of age and older for the prevention of:

- acute and delayed nausea and vomiting associated with initial and repeat courses of highly emetogenic cancer chemotherapy (HEC) including high-dose cisplatin.
- delayed nausea and vomiting associated with initial and repeat courses of moderately emetogenic cancer chemotherapy (MEC).

Limitations of Use

- EMEND has not been studied for the treatment of established nausea and vomiting.

2 DOSAGE AND ADMINISTRATION

2.1 Prevention of Nausea and Vomiting Associated with HEC and MEC in Adult Patients

The recommended dosage of EMEND for injection, dexamethasone, and a 5-HT3 antagonist for the prevention of nausea and vomiting associated with administration of HEC or MEC in adults is shown in Table 1 or Table 2, respectively. Administer EMEND for injection as an intravenous infusion on Day 1 over 20 to 30 minutes, completing the infusion approximately 30 minutes prior to chemotherapy.

Table 1 Recommended Adult Dosing for the Prevention of Nausea and Vomiting Associated with HEC
 | Day 1 | Day 2 | Day 3 | Day 4
EMEND for injection | 150 mg intravenously over 20 to 30 minutes | none | none | none
Dexamethasone [Administer dexamethasone 30 minutes prior to chemotherapy treatment on Day 1 and in the morning on Days 2 through 4. Also administer dexamethasone in the evenings on Days 3 and 4. A 50% dosage reduction of dexamethasone on Days 1 and 2 is recommended to account for a drug interaction with EMEND [see Clinical Pharmacology (12.3)].] | 12 mg orally | 8 mg orally | 8 mg orally twice daily | 8 mg orally twice daily
5-HT3 antagonist | See selected 5-HT3 antagonist prescribing information for the recommended dosage | none | none | none

Table 2 Recommended Adult Dosing for the Prevention of Nausea and Vomiting Associated with MEC
 | Day 1
EMEND for injection | 150 mg intravenously over 20 to 30 minutes
Dexamethasone [Administer dexamethasone 30 minutes prior to chemotherapy treatment on Day 1. A 50% dosage reduction of dexamethasone is recommended to account for a drug interaction with EMEND [see Clinical Pharmacology (12.3)].] | 12 mg orally
5-HT3 antagonist | See selected 5-HT3 antagonist prescribing information for the recommended dosage

2.2 Prevention of Nausea and Vomiting Associated with HEC and MEC in Pediatric Patients

The recommended pediatric dosage regimens of EMEND, to be administered with a 5-HT3 antagonist, with or without a corticosteroid, for the prevention of nausea and vomiting associated with administration of single or multi-day chemotherapy regimens of HEC or MEC, are shown in Tables 3 and 4. Single-day chemotherapy regimens include regimens in which HEC or MEC is administered for a single day only. Multi-day chemotherapy regimens include chemotherapy regimens in which HEC or MEC is administered for 2 or more days.

EMEND Dosage Regimens for Use with Single-Day Chemotherapy Regimens

For pediatric patients weighing at least 6 kg receiving single-day HEC or MEC, EMEND may be administered as:

- a single dose regimen of EMEND for injection infused through a central venous catheter on Day 1, as shown in Table 3; or
- as a 3-day EMEND regimen consisting of EMEND for injection as an intravenous infusion through a central venous catheter on Days 1, 2, and 3. EMEND capsules or EMEND for oral suspension may be used on Days 2 and 3 instead of EMEND for injection, as shown in Table 4.

Administer EMEND for injection on Day 1 over 30 minutes (12 years to 17 years) or 60 minutes (6 months to less than 12 years), completing the infusion approximately 30 minutes prior to chemotherapy.

Table 3 EMEND for Injection Single-Dose Regimen for the Prevention of Nausea and Vomiting Associated with Single-Day Regimens of HEC or MEC in Pediatric Patients 6 Months [Dosing in pediatric patients less than 6 kg is not recommended] to 17 Years
Drug | Age | Regimen
EMEND for injection | 12 Years to 17 Years | 150 mg intravenously over 30 minutes
EMEND for injection | 2 Years to less than 12 Years | 4 mg/kg (maximum dose 150 mg) intravenously over 60 minutes
EMEND for injection | 6 Months to less than 2 Years | 5 mg/kg (maximum dose 150 mg) intravenously over 60 minutes
Dexamethasone [Administer dexamethasone 30 minutes prior to chemotherapy treatment on Day 1] | 6 Months to 17 Years | If a corticosteroid, such as dexamethasone, is co-administered, administer 50% of the recommended corticosteroid dose on Days 1 and 2.
5-HT3 antagonist | 6 Months to 17 Years | See selected 5-HT3 antagonist prescribing information for the recommended dosage

EMEND Dosage Regimen for Use with Multi-Day Chemotherapy Regimens

For pediatric patients weighing at least 6 kg receiving multi-day regimens of HEC or MEC, administer EMEND on Days 1, 2, and 3. Administer EMEND for injection as an intravenous infusion through a central venous catheter on Days 1, 2, and 3. EMEND capsules or EMEND for oral suspension may be used on Days 2 and 3 instead of EMEND for injection, as shown in Table 4.

Administer EMEND for injection over 30 minutes (12 years to 17 years) or 60 minutes (6 months to less than 12 years), completing the infusion approximately 30 minutes prior to chemotherapy.

Table 4 3-Day EMEND Dosage Regimen for Prevention of Nausea and Vomiting Associated with Single- or Multi-day Regimens of HEC or MEC in Pediatric Patients 6 Months [Dosing in pediatric patients less than 6 kg is not recommended.] to 17 Years
 | Age of Pediatric Population | Day 1 | Day 2 | Day 3
EMEND for injection | 12 years to 17 years | 115 mg intravenously over 30 minutes | 80 mg intravenously over 30 minutes OR 80 mg orally (EMEND capsules) [For patients 12 years to 17 years unable to swallow oral capsules, EMEND for oral suspension can be used instead on Days 2 and 3.] | 80 mg intravenously over 30 minutes OR 80 mg orally (EMEND capsules)
 | 6 months to less than 12 years | 3 mg/kg intravenously over 60 minutes (maximum dose 115 mg) | 2 mg/kg intravenously over 60 minutes OR 2 mg/kg orally (EMEND for oral suspension) [For patients less than 12 years of age who weigh at least 40 kg and who are able to swallow oral capsules, EMEND capsules can be used instead on Days 2 and 3.] (maximum dose 80 mg) | 2 mg/kg intravenously over 60 minutes OR 2 mg/kg orally (EMEND for oral suspension) (maximum dose 80 mg)
Dexamethasone [Administer dexamethasone 30 minutes prior to chemotherapy treatment on Day 1.] | 6 months to 17 years | If a corticosteroid, such as dexamethasone, is co-administered, administer 50% of the recommended corticosteroid dose on Days 1 through 4.
5-HT3 antagonist | 6 months to 17 years | See selected 5-HT3 antagonist prescribing information for the recommended dosage.

2.3 Preparation of EMEND for injection

Table 5 Preparation Instructions for EMEND for injection (150 mg)
Step 1 | Aseptically inject 5 mL 0.9% Sodium Chloride Injection, USP into the vial. Assure that 0.9% Sodium Chloride Injection, USP is added to the vial along the vial wall in order to prevent foaming. Swirl the vial gently. Avoid shaking and jetting 0.9% Sodium Chloride Injection, USP into the vial.
Step 2 | Aseptically prepare an infusion bag filled with 145 mL of 0.9% Sodium Chloride Injection, USP.
Step 3 | Aseptically withdraw the entire volume from the vial and transfer it into the infusion bag containing 145 mL of 0.9% Sodium Chloride Injection, USP to yield a total volume of 150 mL and a final concentration of 1 mg/mL.
Step 4 | Gently invert the bag 2 to 3 times.
Step 5 | Determine the volume to be administered from this prepared infusion bag, based on the recommended dose [see Dosage and Administration (2.1, 2.2)]. Adults The entire volume of the prepared infusion bag (150 mL) should be administered. Pediatrics In patients 12 years and older, the volume to be administered is calculated as follows:; - Volume to administer (mL) equals the recommended dose (mg); In patients 6 months to less than 12 years, the volume to be administered is calculated as follows:; - Volume to administer (mL) = recommended dose (mg/kg) × weight (kg) - Note: Do not exceed the maximum dose [see Dosage and Administration (2.2)]; In pediatric patients, the entire volume in the infusion bag may not be required.
Step 6 | If necessary, for volumes less than 150 mL, the calculated volume can be transferred to an appropriate size bag or syringe prior to administration by infusion.
Step 7 | Before administration, inspect the bag for particulate matter and discoloration. Discard the bag if particulate and/or discoloration are observed.
The recommended dose of EMEND for injection is based on the patient's age and weight.

Caution: Do not mix or reconstitute EMEND for injection with solutions for which physical and chemical compatibility have not been established. EMEND for injection is incompatible with any solutions containing divalent cations (e.g., Ca^2+, Mg^2+), including Lactated Ringer's Solution and Hartmann's Solution.

Storage

The reconstituted final drug solution is stable for 24 hours at ambient room temperature [at or below 25°C (77°F)]. Discard unused portion.

3 DOSAGE FORMS AND STRENGTHS

EMEND for injection: 150 mg fosaprepitant, white to off-white lyophilized powder in single-dose glass vial for reconstitution

4 CONTRAINDICATIONS

EMEND is contraindicated in patients:

- who are hypersensitive to any component of the product. Hypersensitivity reactions including anaphylactic reactions, flushing, erythema, and dyspnea have been reported [see Warnings and Precautions (5.2), Adverse Reactions (6.2)].
- taking pimozide. Inhibition of CYP3A4 by aprepitant, the active moiety, could result in elevated plasma concentrations of this drug, which is a CYP3A4 substrate, potentially causing serious or life-threatening reactions, such as QT prolongation, a known adverse reaction of pimozide [see Warnings and Precautions (5.1)].

5 WARNINGS AND PRECAUTIONS

5.1 Clinically Significant CYP3A4 Drug Interactions

Fosaprepitant, a prodrug of aprepitant, is a weak inhibitor of CYP3A4, and aprepitant is a substrate, inhibitor, and inducer of CYP3A4.

- Use of EMEND with other drugs that are CYP3A4 substrates, may result in increased plasma concentration of the concomitant drug.
  - Use of pimozide with EMEND is contraindicated due to the risk of significantly increased plasma concentrations of pimozide, potentially resulting in prolongation of the QT interval, a known adverse reaction of pimozide [see Contraindications (4)].
- Use of EMEND with strong or moderate CYP3A4 inhibitors (e.g., ketoconazole, diltiazem) may increase plasma concentrations of aprepitant and result in an increased risk of adverse reactions related to EMEND.
- Use of EMEND with strong CYP3A4 inducers (e.g., rifampin) may result in a reduction in aprepitant plasma concentrations and decreased efficacy of EMEND.

See Table 7 and Table 8 for a listing of potentially significant drug interactions [see Drug Interactions (7.1, 7.2)].

5.2 Hypersensitivity Reactions

Serious hypersensitivity reactions, including anaphylaxis and anaphylactic shock, during or soon after infusion of fosaprepitant have occurred. Symptoms including flushing, erythema, dyspnea, hypotension and syncope have been reported [see Adverse Reactions (6.2)].

Monitor patients during and after infusion. If hypersensitivity reactions occur, discontinue the infusion and administer appropriate medical therapy. Do not reinitiate EMEND in patients who experience these symptoms with previous use [see Contraindications (4)].

5.3 Infusion Site Reactions

Infusion site reactions (ISRs) have been reported with the use of EMEND for injection [see Adverse Reactions (6.1)]. The majority of severe ISRs, including thrombophlebitis and vasculitis, were reported with concomitant vesicant (anthracycline-based) chemotherapy administration, particularly when associated with extravasation. Necrosis was also reported in some patients with concomitant vesicant chemotherapy. Most ISRs occurred with the first, second or third exposure to single doses of EMEND for injection and in some cases, reactions persisted for two weeks or longer. Treatment of severe ISRs consisted of medical, and in some cases surgical, intervention.

Avoid infusion of EMEND for injection into small veins or through a butterfly catheter. If a severe ISR develops during infusion, discontinue the infusion and administer appropriate medical treatment.

5.4 Decrease in INR with Concomitant Warfarin

Coadministration of EMEND with warfarin, a CYP2C9 substrate, may result in a clinically significant decrease in the International Normalized Ratio (INR) of prothrombin time [see Clinical Pharmacology (12.3)]. Monitor the INR in patients on chronic warfarin therapy in the 2-week period, particularly at 7 to 10 days, following initiation of EMEND with each chemotherapy cycle [see Drug Interactions (7.1)].

5.5 Risk of Reduced Efficacy of Hormonal Contraceptives

Upon coadministration with EMEND, the efficacy of hormonal contraceptives may be reduced during administration of and for 28 days following the last dose of EMEND [see Clinical Pharmacology (12.3)]. Advise patients to use effective alternative or back-up methods of contraception during treatment with EMEND and for 1 month following administration of EMEND [see Drug Interactions (7.1), Use in Specific Populations (8.3)].

6 ADVERSE REACTIONS

The following clinically significant adverse reactions are described elsewhere in the labeling:

- Hypersensitivity Reactions [see Warnings and Precautions (5.2)]
- Infusion Site Reactions [see Warnings and Precautions (5.3)]

6.1 Clinical Trials Experience

Because clinical trials are conducted under widely varying conditions, adverse reaction rates observed in the clinical trials of a drug cannot be directly compared to rates in the clinical trials of another drug and may not reflect the rates observed in clinical practice.

The overall safety of EMEND for injection was evaluated in approximately 1800 adult and pediatric patients.

Adverse Reactions in Adults for the Prevention of Nausea and Vomiting Associated with MEC

In an active-controlled clinical trial in patients receiving MEC, safety was evaluated in 504 patients receiving a single dose of EMEND for injection in combination with ondansetron and dexamethasone (EMEND regimen) compared to 497 patients receiving ondansetron and dexamethasone alone (standard therapy). The most common adverse reactions are listed in Table 6.

Table 6 Most Common Adverse Reactions in Patients Receiving MEC [Reported in ≥2% of patients treated with the EMEND regimen and at a greater incidence than standard therapy.]
 | EMEND for injection, ondansetron, and dexamethasone [EMEND regimen] (N=504) | Ondansetron and dexamethasone [Standard therapy] (N=497)
fatigue | 15% | 13%
diarrhea | 13% | 11%
neutropenia | 8% | 7%
asthenia | 4% | 3%
anemia | 3% | 2%
peripheral neuropathy | 3% | 2%
leukopenia | 2% | 1%
dyspepsia | 2% | 1%
urinary tract infection | 2% | 1%
pain in extremity | 2% | 1%

Infusion-site reactions were reported in 2.2% of patients treated with the EMEND regimen compared to 0.6% of patients treated with standard therapy. The infusion-site reactions included: infusion-site pain (1.2%, 0.4%), injection-site irritation (0.2%, 0.0%), vessel puncture-site pain (0.2%, 0.0%), and infusion-site thrombophlebitis (0.6%, 0.0%), reported in the EMEND regimen compared to standard therapy, respectively.

Adverse Reactions in Adults for the Prevention of Nausea and Vomiting Associated with HEC

In an active-controlled clinical study in patients receiving HEC, safety was evaluated for 1143 patients receiving a single dose of EMEND for injection compared to 1169 patients receiving the 3-day regimen of oral EMEND (aprepitant) [see Clinical Studies (14.1)]. The safety profile was generally similar to that seen in the MEC study with fosaprepitant and prior HEC studies with aprepitant. However, infusion-site reactions occurred at a higher incidence in patients in the fosaprepitant group (3.0%) compared to those in the aprepitant group (0.5%). The following additional infusion-site reactions occurred in the HEC study and were not reported in the MEC study described above: infusion-site erythema (0.5%, 0.1%), infusion-site pruritus (0.3%, 0.0%), and infusion-site induration (0.2%, 0.1%), reported in the fosaprepitant group compared to the aprepitant group, respectively.

Adverse Reactions in Pediatric Patients 6 Months to 17 Years of Age for the Prevention of Nausea and Vomiting Associated with HEC or MEC

Single-Dose EMEND for Injection Regimen

The safety of a single dose of EMEND for injection in pediatric patients (6 months to 17 years) was evaluated in two active-controlled and a single-arm clinical study in patients who received either HEC or MEC. Patients also received ondansetron with or without dexamethasone. The adverse reaction profile was similar to adults. The safety analysis included 69 pediatric patients who received the recommended dose. An additional 70 patients received a single, higher-than-recommended dose. The most common adverse reactions that occurred in >15% of patients who received the recommended dose were anemia, neutropenia, thrombocytopenia, and febrile neutropenia.

3-Day EMEND Regimen

In pediatric patients 12 to 17 years, the safety of the 3-day IV/oral/oral EMEND regimen was evaluated in a single-arm clinical study including 12 patients who received a regimen of either HEC or MEC. In pediatric patients 6 months to 12 years of age, the safety of the 3-day IV/oral/oral EMEND regimen was not directly evaluated. The safety of a single dose of EMEND for injection (3 mg/kg) administered on day 1 of the 3-day IV/oral/oral regimen was evaluated in one active-controlled and one single-arm study including 48 pediatric patients 6 months to 12 years of age who received a regimen of either HEC or MEC.

The safety of the 3-day (IV/IV/IV) regimen of EMEND for injection in pediatric patients (6 months to 17 years) was evaluated in a single-arm clinical study in 100 patients who received either HEC or MEC.

In these clinical studies, pediatric patients also received ondansetron with or without dexamethasone. The adverse reaction profile in pediatric patients was similar to the profile in adult patients receiving a single dose of EMEND for injection.

Because fosaprepitant is converted to aprepitant, those adverse reactions associated with aprepitant might also be expected to occur with EMEND for injection. See the full prescribing information for EMEND capsules for complete safety information regarding studies performed with oral aprepitant.

6.2 Postmarketing Experience

The following adverse reactions have been identified during post-approval use of EMEND. Because these reactions are reported voluntarily from a population of uncertain size, it is not always possible to reliably estimate their frequency or establish a causal relationship to drug exposure.

Skin and subcutaneous tissue disorders: pruritus, rash, urticaria, Stevens-Johnson syndrome/toxic epidermal necrolysis [see Warnings and Precautions (5.2)].

Immune system disorders: hypersensitivity reactions including anaphylaxis and anaphylactic shock [see Contraindications (4), Warnings and Precautions (5.2)].

Nervous system disorders: ifosfamide-induced neurotoxicity reported after EMEND and ifosfamide coadministration.

7 DRUG INTERACTIONS

7.1 Effect of Fosaprepitant/Aprepitant on the Pharmacokinetics of Other Drugs

When administered intravenously, fosaprepitant, a prodrug of aprepitant, is converted to aprepitant within 30 minutes. Therefore, drug interactions following administration of EMEND for injection are likely to occur with drugs that interact with oral aprepitant.

Fosaprepitant, given as a single 150-mg dose, is a weak inhibitor of CYP3A4, and the weak inhibition of CYP3A4 continues for 2 days after single dose administration. Single dose fosaprepitant does not induce CYP3A4. Aprepitant is a substrate, an inhibitor, and an inducer of CYP3A4. Aprepitant is also an inducer of CYP2C9 [see Clinical Pharmacology (12.3)].

Some substrates of CYP3A4 are contraindicated with EMEND [see Contraindications (4)]. Dosage adjustment of some CYP3A4 and CYP2C9 substrates may be warranted, as shown in Table 7.

Table 7 Effects of Fosaprepitant/Aprepitant on the Pharmacokinetics of Other Drugs
CYP3A4 Substrates
Pimozide
Clinical Impact | Increased pimozide exposure
Intervention | EMEND is contraindicated [see Contraindications (4)].
Benzodiazepines
Clinical Impact | Increased exposure to midazolam or other benzodiazepines metabolized via CYP3A4 (alprazolam, triazolam) may increase the risk of adverse reactions [see Clinical Pharmacology (12.3)].
Intervention | Monitor for benzodiazepine-related adverse reactions.
Dexamethasone
Clinical Impact | Increased dexamethasone exposure [see Clinical Pharmacology (12.3)].
Intervention | Reduce the dose of oral dexamethasone by approximately 50% [see Dosage and Administration (2.1)].
Methylprednisolone
Clinical Impact | Increased methylprednisolone exposure [see Clinical Pharmacology (12.3)].
Intervention | Reduce the dose of oral methylprednisolone by approximately 50% on Days 1 and 2 for patients receiving HEC and on Day 1 for patients receiving MEC. Reduce the dose of intravenous methylprednisolone by 25% on Days 1 and 2 for patients receiving HEC and on Day 1 for patients receiving MEC.
Chemotherapeutic agents that are metabolized by CYP3A4
Clinical Impact | Increased exposure of the chemotherapeutic agent may increase the risk of adverse reactions [see Clinical Pharmacology (12.3)].
Intervention | Vinblastine, vincristine, or ifosfamide or other chemotherapeutic agents; - Monitor for chemotherapeutic-related adverse reactions.; Etoposide, vinorelbine, paclitaxel, and docetaxel; - No dosage adjustment needed.
Hormonal Contraceptives
Clinical Impact | Decreased hormonal exposure during administration of and for 28 days after administration of the last dose of EMEND [see Warnings and Precautions (5.5), Use in Specific Populations (8.3), and Clinical Pharmacology (12.3)].
Intervention | Effective alternative or back-up methods of contraception (such as condoms and spermicides) should be used during treatment with EMEND and for 1 month following administration of EMEND.
Examples | birth control pills, skin patches, implants, and certain IUDs
CYP2C9 Substrates
Warfarin
Clinical Impact | Decreased warfarin exposure and decreased prothrombin time (INR) [see Warnings and Precautions (5.4), Clinical Pharmacology (12.3)].
Intervention | In patients on chronic warfarin therapy, monitor the prothrombin time (INR) in the 2-week period, particularly at 7 to 10 days, following administration of EMEND with each chemotherapy cycle.
Other
5-HT3 Antagonists
Clinical Impact | No change in the exposure of the 5-HT3 antagonist [see Clinical Pharmacology (12.3)].
Intervention | No dosage adjustment needed
Examples | ondansetron, granisetron, dolasetron

7.2 Effect of Other Drugs on the Pharmacokinetics of Fosaprepitant/Aprepitant

Aprepitant is a CYP3A4 substrate [see Clinical Pharmacology (12.3)]. Co-administration of EMEND with drugs that are inhibitors or inducers of CYP3A4 may result in increased or decreased plasma concentrations of aprepitant, respectively, as shown in Table 8.

Table 8 Effects of Other Drugs on Pharmacokinetics of Fosaprepitant/Aprepitant
Moderate to Strong CYP3A4 Inhibitors
Clinical Impact | Significantly increased exposure of aprepitant may increase the risk of adverse reactions associated with EMEND [see Adverse Reactions (6.1), Clinical Pharmacology (12.3)].
Intervention | Avoid concomitant use of EMEND
Examples | Moderate inhibitor: diltiazem Strong inhibitors: ketoconazole, itraconazole, nefazodone, troleandomycin, clarithromycin, ritonavir, nelfinavir
Strong CYP3A4 Inducers
Clinical Impact | Substantially decreased exposure of aprepitant in patients chronically taking a strong CYP3A4 inducer may decrease the efficacy of EMEND [see Clinical Pharmacology (12.3)].
Intervention | Avoid concomitant use of EMEND
Examples | rifampin, carbamazepine, phenytoin

8 USE IN SPECIFIC POPULATIONS

8.1 Pregnancy

Risk Summary

There are insufficient data on use of EMEND in pregnant women to inform a drug associated risk. In animal reproduction studies, no adverse developmental effects were observed in rats or rabbits exposed during the period of organogenesis to systemic drug levels (AUC) approximately equivalent to the exposure at the recommended human dose (RHD) of 150 mg [see Data].

The estimated background risk of major birth defects and miscarriage for the indicated populations is unknown. In the U.S. general population, the estimated background risk of major birth defects and miscarriage in clinically recognized pregnancies is 2 to 4% and 15 to 20%, respectively.

Data

Animal Data

In embryofetal development studies in rats and rabbits, aprepitant was administered during the period of organogenesis at oral doses up to 1000 mg/kg twice daily (rats) and up to the maximum tolerated dose of 25 mg/kg/day (rabbits). No embryofetal lethality or malformations were observed at any dose level in either species. The exposures (AUC) in pregnant rats at 1000 mg/kg twice daily and in pregnant rabbits at 25 mg/kg/day were approximately equivalent to the exposure at the RHD of 150 mg. Aprepitant crosses the placenta in rats and rabbits.

8.2 Lactation

Risk Summary

Lactation studies have not been conducted to assess the presence of aprepitant in human milk, the effects on the breastfed infant, or the effects on milk production. Aprepitant is present in rat milk. The developmental and health benefits of breastfeeding should be considered along with the mother's clinical need for EMEND and any potential adverse effects on the breastfed infant from EMEND or from the underlying maternal condition.

8.3 Females and Males of Reproductive Potential

Contraception

Upon administration of EMEND, the efficacy of hormonal contraceptives may be reduced. Advise females of reproductive potential using hormonal contraceptives to use an effective alternative or back-up non-hormonal contraceptive (such as condoms and spermicides) during treatment with EMEND and for 1 month following the last dose [see Drug Interactions (7.1), Clinical Pharmacology (12.3)].

8.4 Pediatric Use

The safety and effectiveness of a single dose and a 3-day regimen of EMEND have been established in pediatric patients 6 months to 17 years for the prevention of acute and delayed nausea and vomiting associated with initial and repeat courses of HEC and MEC.

Use of EMEND in this age group is supported by evidence from adequate and well-controlled studies of EMEND for injection in adults, with additional safety, efficacy and pharmacokinetic data in pediatric patients 6 months to 17 years. Efficacy and safety were also supported by data from an adequate and well-controlled study of a 3-day oral aprepitant regimen in pediatric patients 6 months to 17 years. The safety of the 3-day EMEND for injection regimen in pediatric patients 6 months to 17 years of age was supported by an open-label study in 100 patients receiving HEC or MEC. See the full prescribing information for EMEND capsules for complete clinical information regarding studies performed with oral aprepitant. Adverse reactions were similar to those reported in adult patients [see Dosage and Administration (2.2), Adverse Reactions (6.1), Clinical Pharmacology (12.3)].

The safety and effectiveness of EMEND for the prevention of nausea and vomiting associated with HEC or MEC have not been established in patients less than 6 months of age.

Juvenile Animal Toxicity Data

In juvenile dogs treated with fosaprepitant, changes in reproductive organs were observed. In juvenile rats treated with aprepitant, slight changes in sexual maturation were observed without an effect on reproduction. No effects on neurobehavior, sensory and motor function, or learning and memory were observed in rats.

In a toxicity study in juvenile dogs treated with fosaprepitant from postnatal day 14 (equivalent to a newborn human) to day 42 (approximately equivalent to a 2 year old human), decreased testicular weight and Leydig cell size were seen in the males at 6 mg/kg/day and increased uterine weight, hypertrophy of the uterus and cervix, and edema of vaginal tissues were seen in females from 4 mg/kg/day. A study was also conducted in young rats to evaluate the effects of aprepitant on growth and on neurobehavioral and sexual development. Rats were treated at oral doses up to the maximum feasible dose of 1000 mg/kg twice daily (providing exposure in male and female rats lower than the exposure at the recommended pediatric human dose) from the early postnatal period (Postnatal Day 10 (equivalent to a newborn human) through Postnatal Day 58 (approximately equivalent to a 15 year old human)). Slight changes in the onset of sexual maturation were observed in female and male rats; however, there were no effects on mating, fertility, embryonic-fetal survival, or histomorphology of the reproductive organs. There were no effects in neurobehavioral tests of sensory function, motor function, and learning and memory.

8.5 Geriatric Use

Of the 1649 adult cancer patients treated with intravenous EMEND in HEC and MEC clinical studies, 27% were aged 65 and over, while 5% were aged 75 and over. Other reported clinical experience with EMEND has not identified differences in responses between elderly and younger patients. In general, use caution when dosing elderly patients as they have a greater frequency of decreased hepatic, renal or cardiac function and concomitant disease or other drug therapy [see Clinical Pharmacology (12.3)].

8.6 Patients with Hepatic Impairment

The pharmacokinetics of aprepitant in patients with mild and moderate hepatic impairment were similar to those of healthy subjects with normal hepatic function. No dosage adjustment is necessary for patients with mild to moderate hepatic impairment (Child-Pugh score 5 to 9). There are no clinical or pharmacokinetic data in patients with severe hepatic impairment (Child-Pugh score greater than 9). Therefore, additional monitoring for adverse reactions in these patients may be warranted when EMEND is administered [see Clinical Pharmacology (12.3)].

10 OVERDOSAGE

There is no specific information on the treatment of overdosage with fosaprepitant or aprepitant.

In the event of overdose, EMEND should be discontinued and general supportive treatment and monitoring should be provided. Because of the antiemetic activity of EMEND, drug-induced emesis may not be effective in cases of EMEND overdosage.

Aprepitant is not removed by hemodialysis.

11 DESCRIPTION

EMEND (fosaprepitant) for injection is a sterile, lyophilized formulation containing fosaprepitant dimeglumine, a prodrug of aprepitant, a substance P/neurokinin-1 (NK1) receptor antagonist, an antiemetic agent, chemically described as 1-Deoxy-1-(methylamino)-D-glucitol[3-[[(2R,3S)-2-[(1R)-1-[3,5-bis(trifluoromethyl)phenyl]ethoxy]-3-(4-fluorophenyl)-4-morpholinyl]methyl]-2,5-dihydro-5-oxo-1H-1,2,4-triazol-1-yl]phosphonate (2:1) (salt).

Its empirical formula is C23H22F7N4O6P ∙ 2(C7H17NO5) and its structural formula is:

Fosaprepitant dimeglumine is a white to off-white amorphous powder with a molecular weight of 1004.83. It is freely soluble in water.

Each vial of EMEND for injection for administration as an intravenous infusion contains 150 mg of fosaprepitant (equivalent to 245.3 mg of fosaprepitant dimeglumine) and the following inactive ingredients: edetate disodium (5.4 mg), polysorbate 80 (75 mg), lactose anhydrous (375 mg), sodium hydroxide and/or hydrochloric acid (for pH adjustment).

12 CLINICAL PHARMACOLOGY

12.1 Mechanism of Action

Fosaprepitant is a prodrug of aprepitant and accordingly, its antiemetic effects are attributable to aprepitant.

Aprepitant is a selective high-affinity antagonist of human substance P/neurokinin 1 (NK1) receptors. Aprepitant has little or no affinity for serotonin (5-HT3), dopamine, and corticosteroid receptors, the targets of existing therapies for chemotherapy-induced nausea and vomiting (CINV). Aprepitant has been shown in animal models to inhibit emesis induced by cytotoxic chemotherapeutic agents, such as cisplatin, via central actions. Animal and human Positron Emission Tomography (PET) studies with aprepitant have shown that it crosses the blood brain barrier and occupies brain NK1 receptors. Animal and human studies have shown that aprepitant augments the antiemetic activity of the 5-HT3-receptor antagonist ondansetron and the corticosteroid dexamethasone and inhibits both the acute and delayed phases of cisplatin-induced emesis.

12.2 Pharmacodynamics

Cardiac Electrophysiology

In a randomized, double-blind, positive-controlled, thorough QTc study, a single 200-mg dose of fosaprepitant (approximately 1.3 times the recommended dose) had no effect on the QTc interval.

12.3 Pharmacokinetics

Aprepitant after Fosaprepitant Administration

Following administration of a single intravenous 150-mg dose of fosaprepitant, a prodrug of aprepitant administered as a 20-minute infusion to healthy subjects, the mean AUC0-∞ of aprepitant was 37.4 (± 14.8) mcg∙hr/mL and the mean maximal aprepitant concentration (Cmax) was 4.2 (± 1.2) mcg/mL. Plasma concentrations of fosaprepitant are below the limits of quantification (10 ng/mL) within 30 minutes of the completion of infusion.

Distribution

Aprepitant is greater than 95% bound to plasma proteins. The mean apparent volume of distribution at steady state (Vdss) was approximately 70 L in humans.

Aprepitant crosses the blood brain barrier in humans [see Clinical Pharmacology (12.1)].

Elimination

Metabolism

Fosaprepitant is converted to aprepitant in in vitro incubations with human liver preparations and in S9 preparations from multiple other human tissues including kidney, lung and ileum. Thus, it appears that the conversion of fosaprepitant to aprepitant can occur in multiple extrahepatic tissues in addition to the liver.

Aprepitant undergoes extensive metabolism. In vitro studies using human liver microsomes indicate that aprepitant is metabolized primarily by CYP3A4 with minor metabolism by CYP1A2 and CYP2C19. Metabolism is largely via oxidation at the morpholine ring and its side chains. No metabolism by CYP2D6, CYP2C9, or CYP2E1 was detected.

In healthy young adults, aprepitant accounts for approximately 24% of the radioactivity in plasma over 72 hours following a single oral 300-mg dose of [^14C]-aprepitant, indicating a substantial presence of metabolites in the plasma. Seven metabolites of aprepitant, which are only weakly active, have been identified in human plasma.

Excretion

Following administration of a single intravenous 100-mg dose of [^14C]-fosaprepitant to healthy subjects, 57% of the radioactivity was recovered in urine and 45% in feces.

Aprepitant is eliminated primarily by metabolism; aprepitant is not renally excreted. The apparent terminal half-life ranged from approximately 9 to 13 hours.

Specific Populations

Age: Geriatric Population

Following oral administration of a single 125-mg dose of aprepitant on Day 1 and 80 mg once daily on Days 2 through 5, the AUC0-24hr of aprepitant was 21% higher on Day 1 and 36% higher on Day 5 in elderly (65 years and older) relative to younger adults. The Cmax was 10% higher on Day 1 and 24% higher on Day 5 in elderly relative to younger adults. These differences are not considered clinically meaningful [see Use in Specific Populations (8.5)].

Age: Pediatric Population

Single-Dose EMEND for Injection Regimen: Simulated systemic exposures of aprepitant in patients 2 years to less than 12 years and observed systemic exposures in patients 6 months to less than 2 years and 12 to 17 years are shown in Table 9, including AUC0-24hr, peak plasma concentration (Cmax) on Day 1 and concentrations at the end of Day 1 (C24), Day 2 (C48) and Day 3 (C72).

Table 9 Systemic Exposures of Aprepitant for Single-Dose EMEND for Injection Regimen in Pediatric Patients
Population | Single-Dose of EMEND for Injection Regimen | Geometric Mean
Population | Single-Dose of EMEND for Injection Regimen | AUC 0-24hr. (mcg*hr/mL) | Cmax (mcg/mL) | C24 (mcg/mL) | C48 (mcg/mL) | C72 (mcg/mL)
12 Years to 17 Years | 150 mg | 29.4 | 3.4 | 0.7 | ND [ND = Not Determined. Pharmacokinetic samples were not collected to support the parameter value of interest.] | ND
6 Years to less than 12 Years | 4 mg/kg | 35.2 | 3.6 | 0.7 | 0.2 | 0.05
2 Years to less than 6 Years |  | 28.2 | 3.1 | 0.4 | 0.1 | 0.02
6 Months to less than 2 Years | 5 mg/kg | 32.7 | 3.3 | 0.4 | NE [NE = Not Estimated. The geometric mean could not be estimated due to values being below the limitation of quantification.] | ND

3-Day IV/Oral/Oral EMEND Regimen: Simulated aprepitant systemic exposures in patients 6 months to less than 12 years and observed systemic exposures in patients 12 to 17 years are shown in Table 10, including AUC0-24hr, peak plasma concentration (Cmax) on Day 1 and concentrations at the end of Day 1 (C24), Day 2 (C48) and Day 3 (C72).

Table 10 Systemic Exposures of Aprepitant for 3-Day IV/Oral/Oral Regimen in Pediatric Patients
Population | 3-Day Dose of EMEND (IV/Oral/Oral [IV on Day 1, Oral on Day 2, and Oral on Day 3]) | Geometric Mean
Population | 3-Day Dose of EMEND (IV/Oral/Oral [IV on Day 1, Oral on Day 2, and Oral on Day 3]) | AUC 0-24hr. (mcg*hr/mL) | Cmax (mcg/mL) | C24 (mcg/mL) | C48 (mcg/mL) | C72 (mcg/mL)
12 Years to 17 Years | 115/80/80 mg | 18.0 | 3.0 | 0.4 | 0.2 | NE [NE = Not Estimated. The geometric mean could not be estimated due to values being below the limitation of quantification.]
6 Years to less than 12 Years | 3/2/2 mg/kg | 25.7 | 2.7 | 0.5 | 0.3 | 0.3
2 Years to less than 6 Years |  | 20.2 | 2.3 | 0.3 | 0.2 | 0.2
6 Months to less than 2 Years |  | 16.6 | 1.9 | 0.2 | 0.1 | 0.1

3-Day IV/IV/IV EMEND Regimen: Simulated aprepitant systemic exposures in patients 6 months to 17 years are shown in Table 11, including AUC0-24hr, peak plasma concentration (Cmax) on Day 1 and concentrations at the end of Day 1 (C24), Day 2 (C48), and Day 3 (C72).

Table 11 Systemic Exposures of Aprepitant for 3-Day IV/IV/IV Regimen in Pediatric Patients
Population | 3-Day Dose of EMEND (IV/IV/IV) [IV on Day 1, Day 2, and Day 3] | Geometric Mean
Population | 3-Day Dose of EMEND (IV/IV/IV) [IV on Day 1, Day 2, and Day 3] | AUC 0-24hr. (mcghr/mL) | Cmax (mcg/mL) | C24 (mcg/mL) | C48 (mcg/mL) | C72 (mcg/mL)
12 Years to 17 Years | 115/80/80 mg | 21.1 | 2.5 | 0.4 | 0.4 | 0.4
6 Years to less than 12 Years | 3/2/2 mg/kg | 25.6 | 2.7 | 0.5 | 0.4 | 0.4
2 Years to less than 6 Years |  | 20.3 | 2.3 | 0.3 | 0.2 | 0.2
6 Months to less than 2 Years |  | 16.7 | 1.9 | 0.2 | 0.2 | 0.2

Plasma concentrations of fosaprepitant are negligible within 15 – 30 minutes after the completion of the infusion in pediatric patients.

Sex

Following oral administration of a single dose of aprepitant, ranging from 40 mg to 375 mg, the AUC0-24hr and Cmax are 9% and 17% higher in females as compared with males. The half-life of aprepitant is approximately 25% lower in females as compared with males and Tmax occurs at approximately the same time. These differences are not considered clinically meaningful. A population pharmacokinetic analysis of aprepitant in pediatric patients (6 months to 17 years) suggests that sex has no clinically meaningful effect on the pharmacokinetics of aprepitant.

Race/Ethnicity

Following oral administration of a single dose of aprepitant, ranging from 40 mg to 375 mg, the AUC0-24hr and Cmax are approximately 27% and 19% higher in Hispanics as compared with Caucasians. The AUC0-24hr and Cmax were 74% and 47% higher in Asians as compared to Caucasians. There was no difference in AUC0-24hr or Cmax between Caucasians and Blacks. These differences are not considered clinically meaningful. A population pharmacokinetic analysis of aprepitant in pediatric patients (6 months to 17 years) suggests that race has no clinically meaningful effect on the pharmacokinetics of aprepitant.

Renal Impairment

A single 240-mg oral dose of aprepitant was administered to patients with severe renal impairment (creatinine clearance less than 30 mL/min/1.73 m^2 as measured by 24-hour urinary creatinine clearance) and to patients with end stage renal disease (ESRD) requiring hemodialysis.

In patients with severe renal impairment, the AUC0-∞ of total aprepitant (unbound and protein bound) decreased by 21% and Cmax decreased by 32%, relative to healthy subjects (creatinine clearance greater than 80 mL/min estimated by Cockcroft-Gault method). In patients with ESRD undergoing hemodialysis, the AUC0-∞ of total aprepitant decreased by 42% and Cmax decreased by 32%. Due to modest decreases in protein binding of aprepitant in patients with renal disease, the AUC of pharmacologically active unbound drug was not significantly affected in patients with renal impairment compared with healthy subjects. Hemodialysis conducted 4 or 48 hours after dosing had no significant effect on the pharmacokinetics of aprepitant; less than 0.2% of the dose was recovered in the dialysate.

Hepatic Impairment

Fosaprepitant is metabolized in various extrahepatic tissues; therefore hepatic impairment is not expected to alter the conversion of fosaprepitant to aprepitant.

Following administration of a single 125-mg oral dose of aprepitant on Day 1 and 80 mg once daily on Days 2 and 3 to patients with mild hepatic impairment (Child-Pugh score 5 to 6), the AUC0-24hr of aprepitant was 11% lower on Day 1 and 36% lower on Day 3, as compared with healthy subjects given the same regimen. In patients with moderate hepatic impairment (Child-Pugh score 7 to 9), the AUC0-24hr of aprepitant was 10% higher on Day 1 and 18% higher on Day 3, as compared with healthy subjects given the same regimen. These differences in AUC0-24hr are not considered clinically meaningful. There are no clinical or pharmacokinetic data in patients with severe hepatic impairment (Child-Pugh score greater than 9) [see Use in Specific Populations (8.6)].

Body Mass Index (BMI)

For every 5 kg/m^2 increase in BMI, AUC0-24hr and Cmax of aprepitant decrease by 9% and 10%. BMI of subjects in the analysis ranged from 18 kg/m^2 to 36 kg/m^2. This change is not considered clinically meaningful.

Drug Interactions Studies

Fosaprepitant, given as a single 150-mg dose, is a weak inhibitor of CYP3A4, with no evidence of inhibition or induction of CYP3A4 observed on Day 4. The weak inhibition of CYP3A4 continues for 2 days after single dose administration of fosaprepitant. Aprepitant is a substrate, an inhibitor, and an inducer of CYP3A4. Aprepitant is also an inducer of CYP2C9.

Fosaprepitant or aprepitant is unlikely to interact with drugs that are substrates for the P-glycoprotein transporter.

Effects of Fosaprepitant/Aprepitant on the Pharmacokinetics of Other Drugs

CYP3A4 Substrates

Midazolam: Fosaprepitant 150 mg administered as a single intravenous dose on Day 1 increased the AUC0-∞ of midazolam by approximately 1.8-fold on Day 1 and had no effect on Day 4 when midazolam was coadministered as a single oral dose of 2 mg on Days 1 and 4 [see Drug Interactions (7.1)].

Corticosteroids:

Dexamethasone: Fosaprepitant administered as a single 150 mg intravenous dose on Day 1 increased the AUC0-24hr of dexamethasone, administered as a single 8-mg oral dose on Days 1, 2, and 3, by approximately 2-fold on Days 1 and 2 [see Dosage and Administration (2.1), Drug Interactions (7.1)].

Methylprednisolone: When oral aprepitant as a 3-day regimen (125-mg/80-mg/80-mg) was administered with intravenous methylprednisolone 125 mg on Day 1 and oral methylprednisolone 40 mg on Days 2 and 3, the AUC of methylprednisolone was increased by 1.34-fold on Day 1 and by 2.5-fold on Day 3 [see Drug Interactions (7.1)].

Chemotherapeutic agents:

Docetaxel: In a pharmacokinetic study, oral aprepitant administered as a 3-day regimen (125-mg/80-mg/80-mg) did not influence the pharmacokinetics of docetaxel.

Vinorelbine: In a pharmacokinetic study, oral aprepitant administered as a 3-day regimen (125-mg/80-mg/80-mg) did not influence the pharmacokinetics of vinorelbine to a clinically significant degree.

Oral contraceptives: When oral aprepitant was administered as a 3-day regimen (125-mg/80-mg/80-mg) with ondansetron and dexamethasone, and coadministered with an oral contraceptive containing ethinyl estradiol and norethindrone, the trough concentrations of both ethinyl estradiol and norethindrone were reduced by as much as 64% for 3 weeks post-treatment [see Drug Interactions (7.1)].

CYP2C9 substrates (Warfarin, Tolbutamide):

Warfarin: A single 125-mg dose of oral aprepitant was administered on Day 1 and 80 mg/day on Days 2 and 3 to subjects who were stabilized on chronic warfarin therapy. Although there was no effect of oral aprepitant on the plasma AUC of R(+) or S(-) warfarin determined on Day 3, there was a 34% decrease in S(-) warfarin trough concentration accompanied by a 14% decrease in the prothrombin time (reported as International Normalized Ratio or INR) 5 days after completion of dosing with oral aprepitant [see Drug Interactions (7.1)].

Tolbutamide: Oral aprepitant, when given as 125 mg on Day 1 and 80 mg/day on Days 2 and 3, decreased the AUC of tolbutamide by 23% on Day 4, 28% on Day 8, and 15% on Day 15, when a single dose of tolbutamide 500 mg was administered prior to the administration of the 3-day regimen of oral aprepitant and on Days 4, 8, and 15. This effect was not considered clinically important.

Other Drugs

P-glycoprotein substrates: Aprepitant is unlikely to interact with drugs that are substrates for the P-glycoprotein transporter, as demonstrated by the lack of interaction of oral aprepitant with digoxin in a clinical drug interaction study.

5-HT3 antagonists: In clinical drug interaction studies, aprepitant did not have clinically important effects on the pharmacokinetics of ondansetron, granisetron, or hydrodolasetron (the active metabolite of dolasetron).

Effect of Other Drugs on the Pharmacokinetics of Fosaprepitant/Aprepitant

Rifampin: When a single 375-mg dose of oral aprepitant was administered on Day 9 of a 14-day regimen of 600 mg/day of rifampin, a strong CYP3A4 inducer, the AUC of aprepitant decreased approximately 11-fold and the mean terminal half-life decreased approximately 3-fold [see Drug Interactions (7.2)].

Ketoconazole: When a single 125-mg dose of oral aprepitant was administered on Day 5 of a 10-day regimen of 400 mg/day of ketoconazole, a strong CYP3A4 inhibitor, the AUC of aprepitant increased approximately 5-fold and the mean terminal half-life of aprepitant increased approximately 3-fold [see Drug Interactions (7.2)].

Diltiazem: In a study in 10 patients with mild to moderate hypertension, administration of 100 mg of fosaprepitant as an intravenous infusion with 120 mg of diltiazem, a moderate CYP3A4 inhibitor administered three times daily, resulted in a 1.5-fold increase in the aprepitant AUC and a 1.4-fold increase in the diltiazem AUC.

When fosaprepitant was administered with diltiazem, the mean maximum decrease in diastolic blood pressure was significantly greater than that observed with diltiazem alone [24.3 ± 10.2 mm Hg with fosaprepitant versus 15.6 ± 4.1 mm Hg without fosaprepitant]. The mean maximum decrease in systolic blood pressure was also greater after co-administration of diltiazem with fosaprepitant than administration of diltiazem alone [29.5 ± 7.9 mm Hg with fosaprepitant versus 23.8 ± 4.8 mm Hg without fosaprepitant]. Co-administration of fosaprepitant and diltiazem; however, did not result in any additional clinically significant changes in heart rate or PR interval, beyond those changes observed with diltiazem alone [see Drug Interactions (7.2)].

Paroxetine: Coadministration of once daily doses of oral aprepitant 170 mg, with paroxetine 20 mg once daily, resulted in a decrease in AUC by approximately 25% and Cmax by approximately 20% of both aprepitant and paroxetine. This effect was not considered clinically important.

13 NONCLINICAL TOXICOLOGY

13.1 Carcinogenesis, Mutagenesis, Impairment of Fertility

Carcinogenesis

Carcinogenicity studies were conducted in Sprague-Dawley rats and in CD-1 mice for 2 years. In the rat carcinogenicity studies, animals were treated with oral doses ranging from 0.05 to 1000 mg/kg twice daily. The highest dose produced systemic exposures to aprepitant approximately equivalent to (female rats) or less than (male rats) the adult human exposure at the RHD of 150 mg. Treatment with aprepitant at doses of 5 to 1000 mg/kg twice daily caused an increase in the incidences of thyroid follicular cell adenomas and carcinomas in male rats. In female rats, it produced hepatocellular adenomas at 5 to 1000 mg/kg twice daily and hepatocellular carcinomas and thyroid follicular cell adenomas at 125 to 1000 mg/kg twice daily. In the mouse carcinogenicity studies, the animals were treated with oral doses ranging from 2.5 to 2000 mg/kg/day. The highest dose produced a systemic exposure approximately 2 times the adult human exposure at the RHD of 150 mg. Treatment with aprepitant produced skin fibrosarcomas at 125 and 500 mg/kg/day doses in male mice. Carcinogenicity studies were not conducted with fosaprepitant.

Mutagenesis

Aprepitant and fosaprepitant were not genotoxic in the Ames test, the human lymphoblastoid cell (TK6) mutagenesis test, the rat hepatocyte DNA strand break test, the Chinese hamster ovary (CHO) cell chromosome aberration test and the mouse micronucleus test.

Impairment of Fertility

Fosaprepitant, when administered intravenously, is rapidly converted to aprepitant. In the fertility studies conducted with fosaprepitant and aprepitant, the highest systemic exposures to aprepitant were obtained following oral administration of aprepitant. Oral aprepitant did not affect the fertility or general reproductive performance of male or female rats at doses up to the maximum feasible dose of 1000 mg/kg twice daily (providing exposure in male rats lower than the exposure at the recommended adult human dose of 150 mg and exposure in female rats approximately equivalent to the adult human exposure).

14 CLINICAL STUDIES

14.1 Prevention of Nausea and Vomiting Associated with HEC in Adults

In a randomized, parallel, double-blind, active-controlled study, EMEND for injection 150 mg as a single intravenous infusion (N=1147) was compared to a 3-day oral EMEND regimen (N=1175) in patients receiving a HEC regimen that included cisplatin (≥70 mg/m^2). All patients in both groups received dexamethasone and ondansetron (see Table 12). Patient demographics were similar between the two treatment groups. Of the total 2322 patients, 63% were men, 56% White, 26% Asian, 3% American Indian/Alaska Native, 2% Black, 13% Multi-Racial, and 33% Hispanic/Latino ethnicity. Patient ages ranged from 19 to 86 years of age, with a mean age of 56 years. Other concomitant chemotherapy agents commonly administered were fluorouracil (17%), gemcitabine (16%), paclitaxel (15%), and etoposide (12%).

Table 12 Treatment Regimens in Adult HEC Trial [EMEND for injection placebo, EMEND capsules placebo and dexamethasone placebo (in the evenings on Days 3 and 4) were used to maintain blinding.]
 | Day 1 | Day 2 | Day 3 | Day 4
EMEND Regimen
EMEND for injection | 150 mg intravenously over 20 to 30 minutes approximately 30 minutes prior to chemotherapy | none | none | none
Oral dexamethasone [Dexamethasone was administered 30 minutes prior to chemotherapy treatment on Day 1 and in the morning on Days 2 through 4. Dexamethasone was also administered in the evenings on Days 3 and 4. The 12 mg dose of dexamethasone on Day 1 and the 8 mg once daily dose on Day 2 reflects a dosage adjustment to account for a drug interaction with the EMEND for injection regimen [see Clinical Pharmacology (12.3)].] | 12 mg | 8 mg | 8 mg twice daily | 8 mg twice daily
Ondansetron | Ondansetron [Ondansetron 32 mg intravenous was used in the clinical trials of EMEND. Although this dose was used in clinical trials, this is no longer the currently recommended dose. Refer to the ondansetron prescribing information for the current recommended dose.] | none | none | none
Oral EMEND Regimen
EMEND capsules | 125 mg | 80 mg | 80 mg | none
Oral dexamethasone [Dexamethasone was administered 30 minutes prior to chemotherapy treatment on Day 1 and in the morning on Days 2 through 4. The 12 mg dose of dexamethasone on Day 1 and the 8 mg once daily dose on Days 2 through 4 reflects a dosage adjustment to account for a drug interaction with the oral EMEND regimen [see Clinical Pharmacology (12.3)].] | 12 mg | 8 mg | 8 mg | 8 mg
Ondansetron | Ondansetron | none | none | none

The efficacy of EMEND for injection was evaluated based on the primary and secondary endpoints listed in Table 13 and was shown to be non-inferior to that of the 3-day oral aprepitant regimen with regard to complete response in each of the evaluated phases. The pre-specified non-inferiority margin for complete response in the overall phase was 7%. The pre-specified non-inferiority margin for complete response in the delayed phase was 7.3%. The pre-specified non-inferiority margin for no vomiting in the overall phase was 8.2%.

Table 13 Percent of Adult Patients Receiving HEC Responding by Treatment Group and Phase — Cycle 1
ENDPOINTS | EMEND for Injection Regimen (N = 1106) [N: Number of patients included in the primary analysis of complete response.] % | Oral EMEND Regimen (N = 1134) % | Difference [Difference and Confidence interval (CI) were calculated using the method proposed by Miettinen and Nurminen and adjusted for Gender.] (95% CI)
PRIMARY ENDPOINT
Complete Response [Complete Response = no vomiting and no use of rescue therapy.]
Overall [Overall = 0 to 120 hours post-initiation of cisplatin chemotherapy.] | 71.9 | 72.3 | -0.4 (-4.1, 3.3)
SECONDARY ENDPOINTS
Complete Response
Delayed phase [Delayed phase = 25 to 120 hours post-initiation of cisplatin chemotherapy.] | 74.3 | 74.2 | 0.1 (-3.5, 3.7)
No Vomiting
Overall | 72.9 | 74.6 | -1.7 (-5.3, 2.0)

14.2 Prevention of Nausea and Vomiting Associated with MEC in Adults

In a randomized, parallel, double-blind, active comparator-controlled study, EMEND for injection 150 mg as a single intravenous infusion (N=502) in combination with ondansetron and dexamethasone (EMEND regimen) was compared with ondansetron and dexamethasone alone (standard therapy) (N=498) (see Table 14) in patients receiving a MEC regimen. Patient demographics were similar between the two treatment groups. Of the total 1,000 patients included in the efficacy analysis, 41% were men, 84% White, 4% Asian, 1% American Indian/Alaska Native, 2% Black, 10% Multi-Racial, and 19% Hispanic/Latino ethnicity. Patient ages ranged from 23 to 88 years of age, with a mean age of 60 years. The most commonly administered MEC chemotherapeutic agents were carboplatin (51%), oxaliplatin (24%), and cyclophosphamide (12%).

Table 14 Treatment Regimens in Adult MEC Trial [EMEND for injection placebo and dexamethasone placebo (on Day 1) were used to maintain blinding.]
 | Day 1 | Day 2 | Day 3
EMEND Regimen
EMEND for Injection | 150 mg intravenously over 20 to 30 minutes approximately 30 minutes prior to chemotherapy | none | none
Oral Dexamethasone [Dexamethasone was administered 30 minutes prior to chemotherapy treatment on Day 1. The 12 mg dose reflects a dosage adjustment to account for a drug interaction with the EMEND for injection regimen [see Clinical Pharmacology (12.3)].] | 12 mg | none | none
Oral Ondansetron [The first ondansetron dose was administered 30 to 60 minutes prior to chemotherapy treatment on Day 1 and the second dose was administered 8 hours after first ondansetron dose.] | 8 mg for 2 doses | none | none
Standard Therapy
Oral Dexamethasone | 20 mg | none | none
Oral Ondansetron | 8 mg for 2 doses | 8 mg twice daily | 8 mg twice daily

The primary endpoint was complete response (defined as no vomiting and no rescue therapy) in the delayed phase (25 to 120 hours) of chemotherapy-induced nausea and vomiting. The results by treatment group are shown in Table 15.

Table 15 Percent of Adult Patients Receiving MEC Responding by Treatment Group
ENDPOINTS | EMEND for Injection Regimen (N = 502) [N: Number of patients included in the intention to treat population.] % | Standard Therapy Regimen (N = 498) % | P-Value | Treatment Difference (95% CI)
PRIMARY ENDPOINT
Complete Response [Complete Response = no vomiting and no use of rescue therapy.]
Delayed phase [Delayed phase = 25 to 120 hours post-initiation of chemotherapy.] | 78.9 | 68.5 | <0.001 | 10.4 (5.1, 15.9)

16 HOW SUPPLIED/STORAGE AND HANDLING

Single-dose glass vial containing 150 mg of fosaprepitant as a white to off-white lyophilized powder for reconstitution. Supplied as follows:

 | NDC 0006-3061-00 | 1 vial per carton.

Storage

Emend for injection vials must be refrigerated, store at 2°C-8°C (36°F-46°F).

The reconstituted final drug solution is stable for 24 hours at ambient room temperature [at or below 25°C (77°F)]. Discard unused portion.

17 PATIENT COUNSELING INFORMATION

Advise the patient to read the FDA-approved patient labeling (Patient Information).

Hypersensitivity

Advise patients that hypersensitivity reactions, including anaphylaxis and anaphylactic shock, have been reported in patients taking EMEND. Advise patients to seek immediate medical attention if they experience signs or symptoms of a hypersensitivity reaction, such as hives, rash and itching, skin peeling or sores, flushing, difficulty in breathing or swallowing, or dizziness, rapid or weak heartbeat or feeling faint [see Warnings and Precautions (5.2)].

Infusion Site Reactions

Advise patients to seek medical attention if they experience new or worsening signs or symptoms of an infusion site reaction, such as erythema, edema, pain, necrosis, vasculitis, or thrombophlebitis at or near the infusion site [see Warnings and Precautions (5.3)].

Drug Interactions

Advise patients to discuss all medications they are taking, including other prescription, non-prescription medication or herbal products [see Contraindications (4), Warnings and Precautions (5.1)].

Warfarin: Instruct patients on chronic warfarin therapy to follow instructions from their healthcare provider regarding blood draws to monitor their INR during the 2-week period, particularly at 7 to 10 days, following initiation of EMEND with each chemotherapy cycle [see Warnings and Precautions (5.4)].

Hormonal Contraceptives: Advise patients that administration of EMEND may reduce the efficacy of hormonal contraceptives. Instruct patients to use effective alternative or back-up methods of contraception (such as condoms and spermicides) during treatment with EMEND and for 1 month following administration of EMEND [see Warnings and Precautions (5.5), Use in Specific Populations (8.3)].

Manufactured for:
Merck Sharp & Dohme LLC, Rahway, NJ 07065, USA

Manufactured by:
Patheon Manufacturing Services LLC, 5900 Martin Luther King Jr. Highway, Greenville, NC 27834, USA

For patent information: www.msd.com/research/patent

Copyright © 2008-2022 Merck & Co., Inc., Rahway, NJ, USA, and its affiliates.
All rights reserved.

uspi-mk0517-iv-edta5-2205r010

Patient Information
EMEND® (EE mend)
(fosaprepitant)
for injection

Read this Patient Information before you start receiving EMEND for injection and each time you are scheduled to receive EMEND for injection. There may be new information. This information does not take the place of talking with your healthcare provider about your medical condition or treatment.

What is EMEND for injection?

EMEND for injection is a prescription medicine used with other medicines that treat nausea and vomiting in patients 6 months of age and older to prevent nausea and vomiting caused by certain anti-cancer (chemotherapy) medicines.

- EMEND for injection is not used to treat nausea and vomiting that you already have.
- It is not known if EMEND for injection is safe and effective in children less than 6 months of age.

Who should not receive EMEND for injection?

Do not receive EMEND for injection if you:

- are allergic to fosaprepitant, aprepitant, or any of the ingredients in EMEND for injection. See the end of this leaflet for a complete list of the ingredients in EMEND for injection.
- are taking pimozide (ORAP®).

What should I tell my healthcare provider before receiving EMEND for injection?

Before receiving EMEND for injection, tell your healthcare provider if you:

- have liver problems.
- are pregnant or plan to become pregnant. It is not known if EMEND for injection can harm your unborn baby.
  - Women who use birth control medicines containing hormones to prevent pregnancy (birth control pills, skin patches, implants, and certain IUDs) should also use a backup method of birth control that does not contain hormones, such as condoms and spermicides, during treatment with EMEND for injection and for 1 month after receiving EMEND for injection.
- are breastfeeding or plan to breastfeed. It is not known if EMEND for injection passes into your breast milk. Talk to your healthcare provider about the best way to feed your baby if you receive EMEND for injection.

Tell your healthcare provider about all the medicines you take, including prescription and over-the-counter medicines, vitamins, and herbal supplements.

EMEND for injection may affect the way other medicines work, and other medicines may affect the way EMEND for injection works, causing serious side effects.

Know the medicines you take. Keep a list of them to show your healthcare provider or pharmacist when you get a new medicine.

How will I receive EMEND for injection?

Adults 18 years of age and older:

EMEND for injection will be given on Day 1 of chemotherapy treatment. It will be given to you by intravenous (IV) infusion in your vein about 50 to 60 minutes before you start your chemotherapy treatment.

Children 6 months to 17 years of age:

EMEND for injection will be given to your child by intravenous (IV) infusion into a large vein through a type of IV line called a central venous catheter, about 1 hour to 1 ½ hours before the start of their chemotherapy treatment. Depending on the chemotherapy treatment, there are 2 ways that EMEND for injection may be given:

1. EMEND for injection is given on Day 1 only (single day of chemotherapy).
2. EMEND for injection is given on Days 1, 2, and 3 (single or multiple days of chemotherapy).
  - Your child may receive capsules of EMEND or an oral suspension of EMEND instead of EMEND for injection on Days 2 and 3. If your child will receive either of these, see the Patient Information for EMEND capsules or EMEND for oral suspension for further information.

If you take the blood thinner medicine warfarin sodium (COUMADIN®, JANTOVEN®), your healthcare provider may do blood tests after you receive EMEND for injection to check your blood clotting.

What are the possible side effects of EMEND for injection?

EMEND for injection may cause serious side effects, including:

- Serious allergic reactions. Allergic reactions can happen with EMEND for injection and may be serious. Tell your doctor or nurse right away if you have hives, rash, itching, flushing or redness of your face or skin, trouble breathing or swallowing, dizziness, a rapid or weak heartbeat, or you feel faint during or soon after you receive EMEND for injection, as you may need emergency medical care.
- Severe skin reactions, which may include rash, skin peeling, or sores, may occur.
- Infusion site reactions (ISR) at or near the infusion site have happened with EMEND for Injection.
  Most severe ISR have happened with a certain type of chemotherapy medicine that can burn or blister your skin (vesicant) with side effects, including pain, swelling and redness. Death of skin tissue (necrosis) has happened in some people getting this type of chemotherapy medicine. Most ISR can happen with the first, second, or third dose and some can last up to 2 weeks or longer. Tell your healthcare provider right away if you get any infusion site side effects.

In adults, the most common side effects of EMEND for injection include:

- tiredness
- diarrhea
- low white blood cell and red blood cell counts
- weakness

- feeling weak or numb in your arms and legs
- painful, difficult, or changes in your digestion (dyspepsia)
- urinary tract infection
- pain in your arms and legs

In children 6 months to 17 years of age, the most common side effects of EMEND for injection include:

- low red blood cell count
- low white blood cell count

- low blood platelet count
- low white blood cell count with a fever

Tell your healthcare provider if you have any side effect that bothers you or that does not go away. These are not all of the possible side effects of EMEND for injection. For more information ask your healthcare provider or pharmacist.

Call your doctor for medical advice about side effects. You may report side effects to FDA at 1-800-FDA-1088.

General information about the safe and effective use of EMEND for injection.

If you would like more information about EMEND for injection, talk with your healthcare provider. You can ask your healthcare provider or pharmacist for information about EMEND for injection that is written for health professionals. For more information about EMEND for injection call 1-800-622-4477 or go to www.emend.com.

What are the ingredients in EMEND for injection?

Active ingredient: fosaprepitant

Inactive ingredients: edetate disodium, polysorbate 80, lactose anhydrous, sodium hydroxide and/or hydrochloric acid (for pH adjustment)

Manufactured for: Merck Sharp & Dohme LLC, Rahway, NJ 07065, USA
Manufactured by: Patheon Manufacturing Services LLC, 5900 Martin Luther King Jr. Highway, Greenville, NC 27834, USA
For patent information: www.msd.com/research/patent
The brands listed in the above sections "Who should not receive EMEND for injection?" and "How will I receive EMEND for injection?" are the registered trademarks of their respective owners and are not trademarks of Merck Sharp & Dohme LLC.
Copyright © 2008-2022 Merck & Co., Inc., Rahway, NJ, USA, and its affiliates.
All rights reserved.
usppi-mk0517-iv-2205r016

This Patient Information has been approved by the U.S. Food and Drug Administration.

Revised: May 2022

PRINCIPAL DISPLAY PANEL - 150 mg Vial Carton

NDC 0006-3061-00

Emend®
(fosaprepitant)
for Injection

150 mg per vial

Reconstitute with 5 mL of 0.9% Sodium
Chloride for Injection.

STERILE LYOPHILIZED POWDER
FOR INTRAVENOUS USE ONLY AFTER
RECONSTITUTION AND DILUTION

DO NOT USE WITH SOLUTIONS
CONTAINING DIVALENT CATIONS
(e.g., Ca^2+, Mg^2+) INCLUDING
LACTATED RINGER'S SOLUTION
AND HARTMANN'S SOLUTION.

Rx only

Single-Dose Vial –
Discard Unused Portion